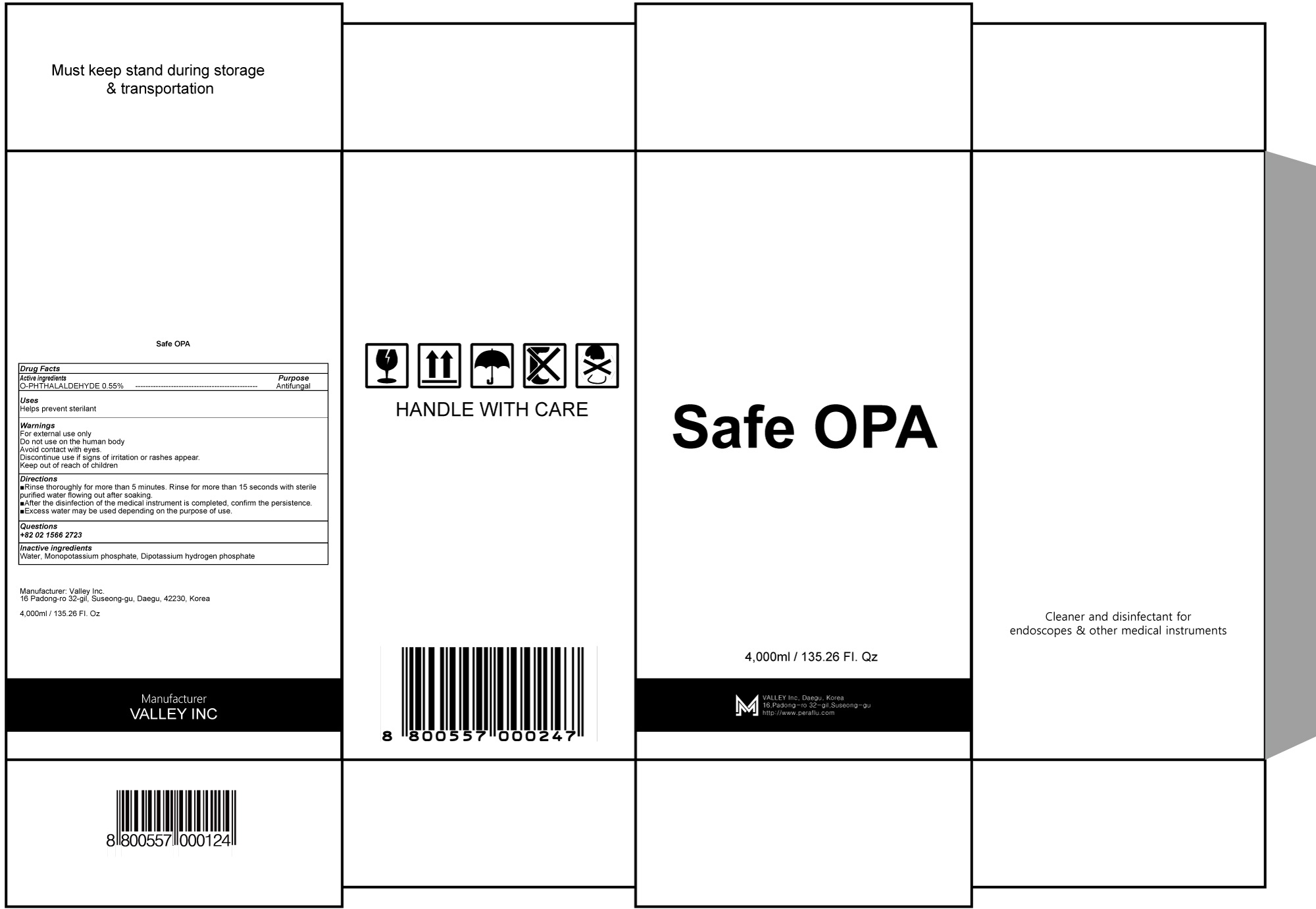 DRUG LABEL: Safe OPA
NDC: 81803-030 | Form: LIQUID
Manufacturer: Valley Inc.
Category: otc | Type: HUMAN OTC DRUG LABEL
Date: 20241209

ACTIVE INGREDIENTS: O-PHTHALALDEHYDE 22 g/4000 mL
INACTIVE INGREDIENTS: WATER; MONOBASIC POTASSIUM PHOSPHATE; DIBASIC POTASSIUM PHOSPHATE

ACTIVE INGREDIENT

O-PHTHALALDEHYDE 0.55%

INACTIVE INGREDIENTS

Water, Monopotassium phosphate, Dipotassium hydrogen phosphate

PURPOSE

Antifungal

WARNINGS

For external use only
Do not use on the human body
Avoid contact with eyes.
Discontinue use if signs of irritation or rashes appear.
Keep out of reach of children

KEEP OUT OF REACH OF CHILDREN

Uses

Helps prevent sterilant

Directions

■Rinse thoroughly for more than 5 minutes. Rinse for more than 15 seconds with sterile purified water flowing out after soaking.
■After the disinfection of the medical instrument is completed, confirm the persistence.
■Excess water may be used depending on the purpose of use.

QUESTIONS

+82 02 1566 2723